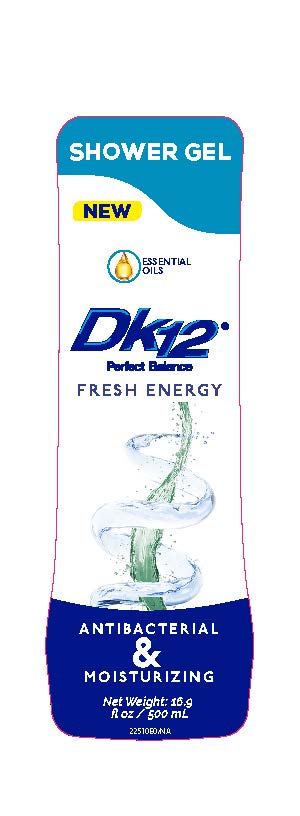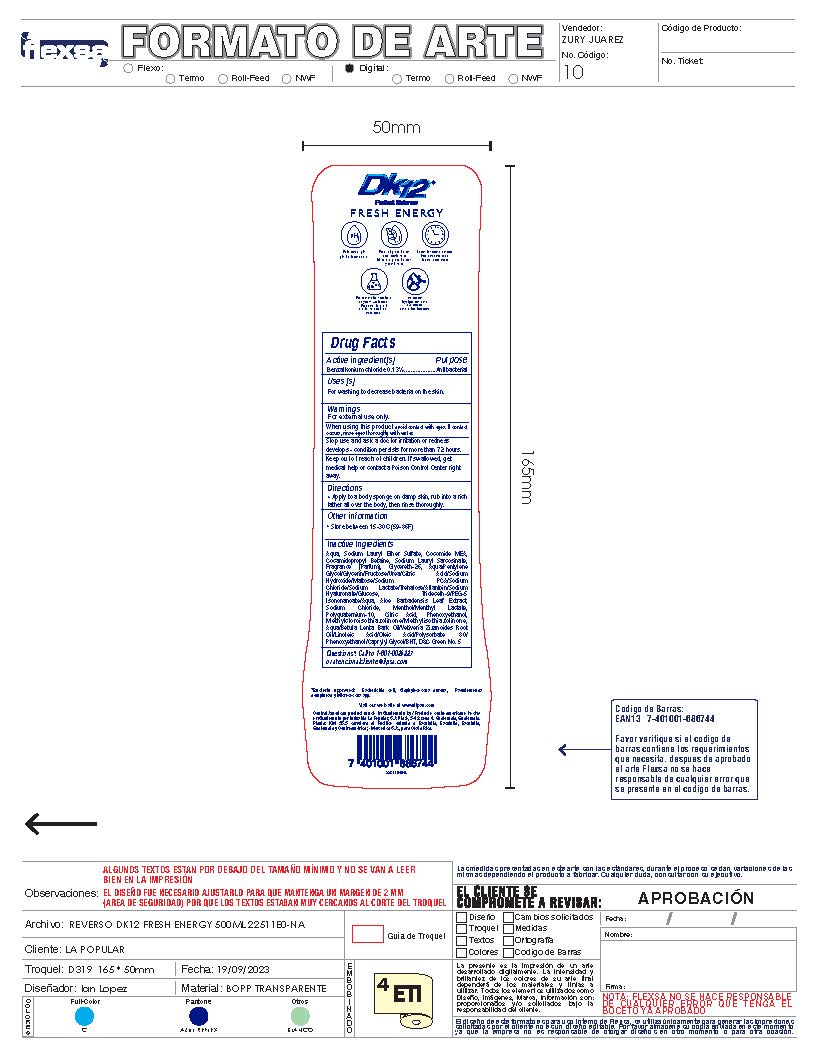 DRUG LABEL: DK12 Shower Gel Fresh Energy
NDC: 62476-011 | Form: GEL
Manufacturer: Industria La Popular, S.A.
Category: otc | Type: HUMAN OTC DRUG LABEL
Date: 20241202

ACTIVE INGREDIENTS: BENZALKONIUM CHLORIDE 0.65 g/500 mL
INACTIVE INGREDIENTS: ALOE VERA LEAF; MENTHOL, UNSPECIFIED FORM; SODIUM LAURYL SARCOSINATE; SODIUM CHLORIDE; MENTHYL LACTATE, (-)-; UREA; TREHALOSE; POLYQUATERNIUM-10 (400 CPS AT 2%); COCAMIDE; METHYLCHLOROISOTHIAZOLINONE; SODIUM LAURYL SULFATE; WATER; GLYCERIN; METHYLISOTHIAZOLINONE; ANHYDROUS CITRIC ACID; D&C GREEN NO. 5; PHENOXYETHANOL; HYALURONATE SODIUM; PROPYLENE GLYCOL; BETULA LENTA BARK; POLYSORBATE 80; PENTYLENE GLYCOL; SODIUM HYDROXIDE; SODIUM LACTATE; SODIUM PIDOLATE; ANHYDROUS DEXTROSE; LINOLEIC ACID; OLEIC ACID; BUTYLATED HYDROXYTOLUENE; ISONONYL ISONONANOATE; TRIDECETH-9; VETIVERIA ZIZANIOIDES ROOT; CAPRYLYL GLYCOL; FRUCTOSE; DISODIUM LAURETH SULFOSUCCINATE; ALLANTOIN; MALTOSE; GLYCERETH-26; COCAMIDOPROPYL BETAINE

DK12 Shower Gel Fresh Energy

Active Ingredient

Benzalkonium Chloride 0.13%

Purpose

Antibacterial

Uses

For washing to decrease bacteria on the skin

Warnings

For External Use only.

When using this product

avoid contact with eyes. If contact occurs, rinse eyes thoroughly with water.

Stop use and ask a doctor

irritation or redness develops - condition persists for more than 72 hours.

Keep out of reach of children.

If swallowed, get medical help or contact a Poison Control Center right away

Directions

Apply to a body sponge on damp skin, rub into a rich lather all over the body, then rinse thoroughly.

Other Information

Store between 15-30C (59-86F)

Inactive Ingredients

Aqua, Sodium Lauryl Ether Sulfate, Cocomide MEA, Cocamidopropyl Betaine, Sodium Lauryl Sarcosinate, Fragrance (Parfum), Glycereth-26, Aqua/Pentylene Glycol/Glycerin/Fructose/Urea/Citric Acid/Sodium

Hydroxide/Maltose/Sodium PCA/Sodium Chloride/Sodium Lactate/Trehalose/Allantoin/Sodium Hyaluronate/Glucose, Trideceth-9/PEG-5 Isononanoate/Aqua, Aloe Barbadensis Leaf Extract,

Sodium Chloride, Menthol/Menthyl Lactate, Polyquaternium-10, Citric Acid, Phenoxyethanol, Methylcloroisothiazolinone/Methylisothiazolinone, Aqua/Betula Lenta Bark Oil/Vetiveria Zizanoides Root Oil/Linoleic Acid/Oleic Acid/Polysorbate 80/Phenoxyethanol/Caprylyl Glycol/BHT, D&C Green No. 5